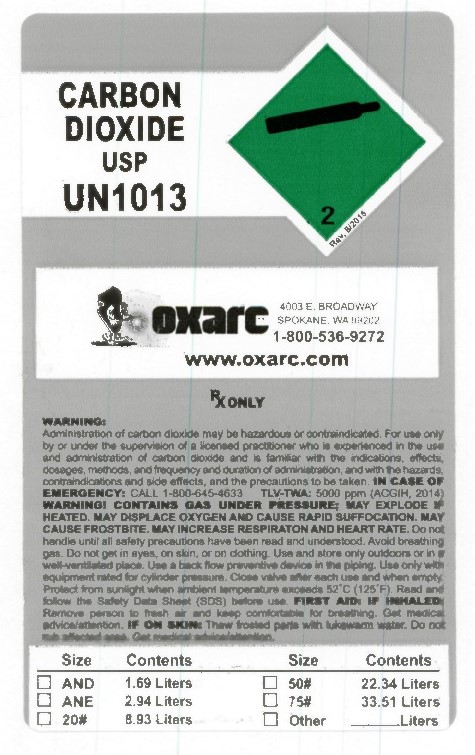 DRUG LABEL: Carbon Dioxide
NDC: 34057-511 | Form: GAS
Manufacturer: Oxarc, LLC
Category: animal | Type: PRESCRIPTION ANIMAL DRUG LABEL
Date: 20251125

ACTIVE INGREDIENTS: CARBON DIOXIDE 990 mL/1 L

carbon dioxide

PACKAGE LABEL

CARBON DIOXIDE USP UN1013
OXARC 4003 E BROADWAY SPOKANE, WA 99202 1-800-536-9272 www.oxarc.com
Rx only WARNING: Administration of Carbon Dioxide may be hazardous or contraindicated. For use only by or under the supervision of a licensed practitioner who is experienced in the use and administration of Carbon Dioxide and is familiar with the indications, effects, dosages, methods, and frequency and duration of administration, and with the hazards, contraindications, and side effects and the precautions to be taken. IN CASE OF EMERGENCY: CALL 1-800-645-4633 TLV-TWA: 5000 ppm (ACGIH, 2014)
WARNING: CONTAINS GAS UNDER PRESSURE; MAY EXPLODE IF HEATED. MAY DISPLACE OXYGEN AND CAUSE RAPID SUFFOCATION. MAY CAUSE FROSTBITE. MAY INCREASE RESPIRATION AND HEART RATE. Do not handle until all safety precautions have been read and understood. Keep and store away from clothing and other combustible materials. Keep valves and fittings free from grease and oil. Use and store only outdoors or in a well-ventilated place. In case of fire: Stop leak if safe to do so. Use a back flow preventive device in the piping. Use only with equipment of compatible materials of construction and rated for cylinder pressure. Use only with equipment cleaned for oxygen service. Open valve slowly. Close valve after each use and when empty. Protect from sunlight when Protect from sunlight when ambient temperature exceeds 52 degrees C (125 degrees F). Read and follow the Safety Data Sheet (SDS) before use. FIRST AID: IF INHALED: Remove person to fresh air and keep comfortable for breathing. Get immediate medical advice/attention. IF ON SKIN: Thaw frosted parts with lukewarm water. Do not rub affected area. Get immediate medical advice/attention. CAS: 124-38-9
DO NOT REMOVE THIS PRODUCT LABEL
Size Contents Size Contents AND 1.69 Liters 50# 22.34 Liters ANE 2.94 Liters 75# 33.51 Liters 20# 8.93